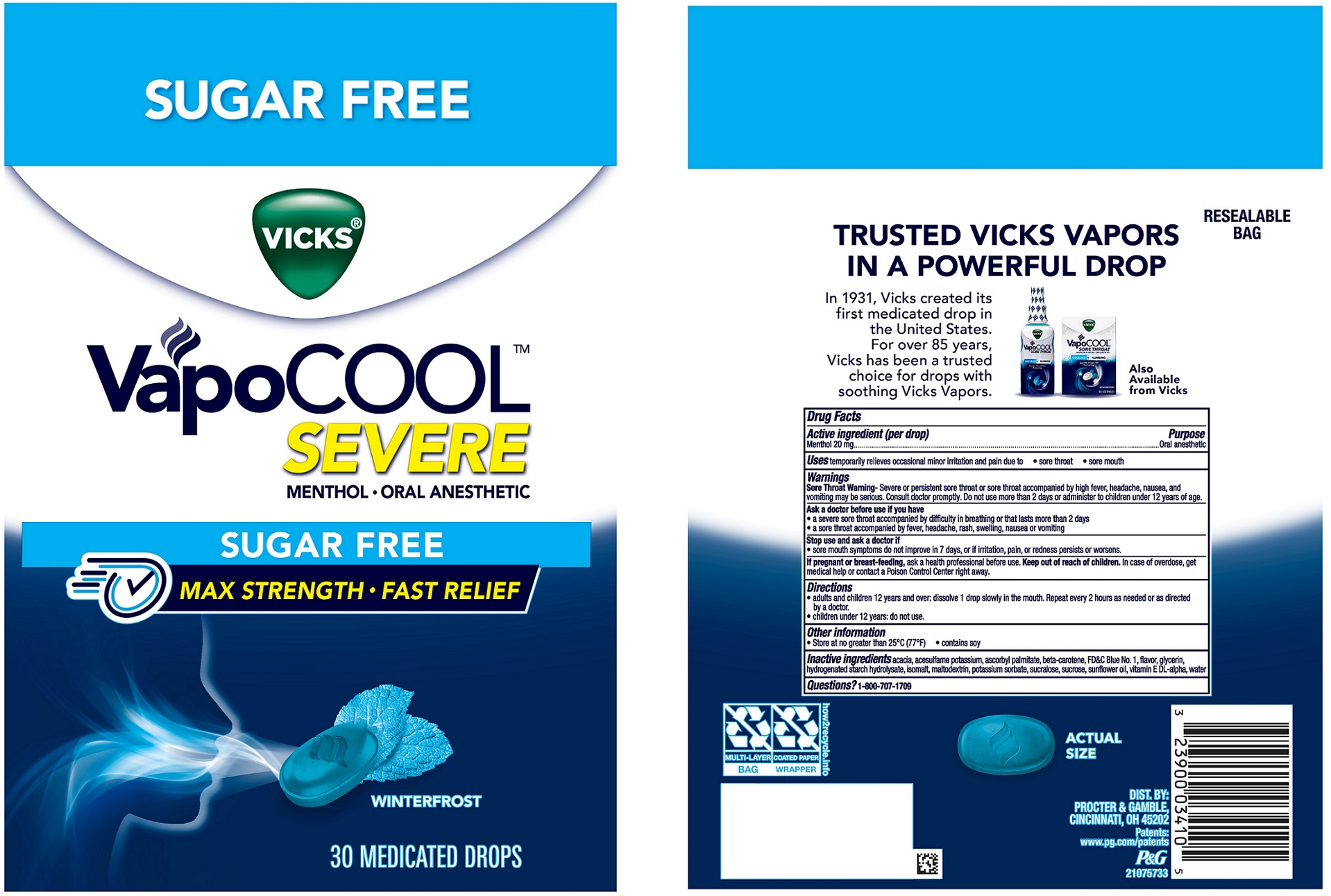 DRUG LABEL: Vicks VapoCOOL
NDC: 84126-313 | Form: LOZENGE
Manufacturer: The Procter & Gamble Manufacturing Company
Category: otc | Type: HUMAN OTC DRUG LABEL
Date: 20251003

ACTIVE INGREDIENTS: MENTHOL 20 mg/1 1
INACTIVE INGREDIENTS: SUCROSE; ACESULFAME POTASSIUM; HYDROGENATED STARCH HYDROLYSATE; ISOMALT; MALTODEXTRIN; ASCORBYL PALMITATE; SUCRALOSE; SUNFLOWER OIL; BETA CAROTENE; ACACIA; POTASSIUM SORBATE; GLYCERIN; FD&C BLUE NO. 1; WATER; .ALPHA.-TOCOPHEROL, DL-

Vicks®VapoCOOL™SEVERE MENTHOL • ORAL ANESTHETIC
SUGAR FREE WINTERFROST MEDICATED DROPS

Drug Facts

Active ingredient (per drop)

Menthol 20 mg

Purpose

Oral anesthetic

Uses

temporarily relieves occasional minor irritation and pain due to

- sore throat
- sore mouth

Warnings

Sore Throat Warning-

Severe or persistent sore throat or sore throat accompanied by high fever, headache, nausea, and vomiting may be serious. Consult doctor promptly. Do not use more than 2 days or administer to children under 12 years of age.

Ask a doctor before use if you have

- a severe sore throat accompanied by difficulty in breathing or that lasts more than 2 days
- a sore throat accompanied by fever, headache, rash, swelling, nausea or vomiting

Stop use and ask a doctor if

- sore mouth symptoms do not improve in 7 days, or if irritation, pain, or redness persists or worsens.

If pregnant or breast-feeding,

ask a health professional before use.

Keep out of reach of children.

OVERDOSAGE

In case of overdose, get medical help or contact a Poison Control Center right away

Directions

- adults and children 12 years and over: dissolve 1 drop slowly in the mouth. Repeat every 2 hours as needed or as directed by a doctor.
- children 12 years and under: do not use

Other information

- Store at no greater than 25°C (77°F)
- contains Soy.

Inactive ingredients

acacia, acesulfame potassium, ascorbyl palmitate, beta-carotene, FD&C Blue No. 1, flavor, glycerin, hydrogenated starch hydrolysate, isomalt, maltodextrin, potassium sorbate, sucralose, sucrose, sunflower oil, vitamin E DL-alpha, water

Questions?

1-800-707-1709

DIST. BY:

PROCTER & GAMBLE

CINCINNATI, OH 45202

PACKAGE LABEL

SUGAR FREE

VICKS ®

VapoCOOL™

SEVERE

MENTHOL - ORAL ANESTHETIC

SUGAR FREE

MAX STRENGTH - FAST RELIEF

WINTERFROST

30 MEDICATED DROPS